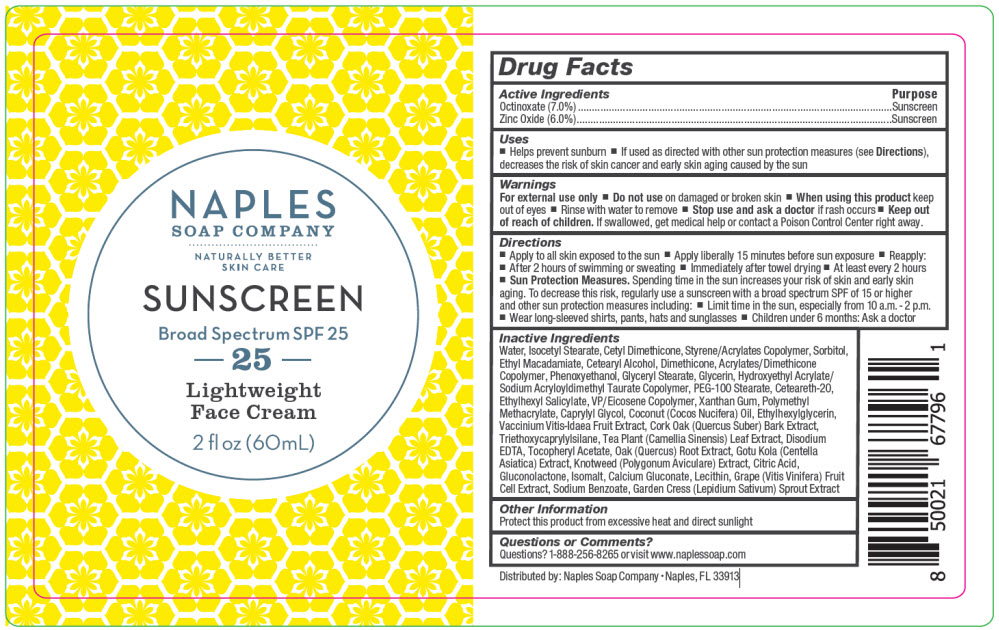 DRUG LABEL: Naples Company - Sunscreen Broad Spectrum SPF 25  Lightweight Face
NDC: 66163-2603 | Form: LOTION
Manufacturer: Cosmetic Solutions LLC
Category: otc | Type: HUMAN OTC DRUG LABEL
Date: 20220607

ACTIVE INGREDIENTS: Octinoxate 7 g/100 mL; Zinc Oxide 6 g/100 mL
INACTIVE INGREDIENTS: Water; Isocetyl Stearate; Sorbitol; Ethyl Macadamiate; Cetostearyl Alcohol; Dimethicone; Phenoxyethanol; Glyceryl Monostearate; Glycerin; Hydroxyethyl Acrylate/Sodium Acryloyldimethyl Taurate Copolymer (100000 MPA.S at 1.5%); PEG-100 Stearate; Polyoxyl 20 Cetostearyl Ether; Octisalate; Xanthan Gum; Poly(Methyl Methacrylate; 450000 MW); Caprylyl Glycol; Ethylhexylglycerin; Lingonberry; Quercus Suber Bark; Triethoxycaprylylsilane; Green Tea Leaf; Edetate Disodium Anhydrous; .Alpha.-Tocopherol Acetate; Centella Asiatica Whole; Polygonum Aviculare Top; Citric Acid Monohydrate; Gluconolactone; Isomalt; Calcium Gluconate; Sodium Benzoate; Garden Cress Sprout

Naples Soap Company - Sunscreen Broad Spectrum SPF 25 Lightweight Face Cream

Drug Facts

ACTIVE INGREDIENT

Active Ingredients | Purpose
Octinoxate (7.0%) | Sunscreen
Zinc Oxide (6.0%) | Sunscreen

Uses

- Helps prevent sunburn
- If used as directed with other sun protection measures (see Directions), decreases the risk of skin cancer and early skin aging caused by the sun

Warnings

For external use only

- Do not use on damaged or broken skin
- When using this product keep out of eyes
- Rinse with water to remove
- Stop use and ask a doctor if rash occurs

- Keep out of reach of children. If swallowed, get medical help or contact a Poison Control Center right away.

Directions

- Apply to all skin exposed to the sun
- Apply liberally 15 minutes before sun exposure
- Reapply:
  - After 2 hours of swimming or sweating
  - Immediately after towel drying
  - At least every 2 hours
- Sun Protection Measures. Spending time in the sun increases your risk of skin and early skin aging. To decrease this risk, regularly use a sunscreen with a broad spectrum SPF of 15 or higher and other sun protection measures including:
  - Limit time in the sun, especially from 10 a.m. - 2 p.m.
  - Wear long-sleeved shirts, pants, hats and sunglasses
- Children under 6 months: Ask a doctor

Inactive Ingredients

Water, Isocetyl Stearate, Cetyl Dimethicone, Styrene/Acrylates Copolymer, Sorbitol, Ethyl Macadamiate, Cetearyl Alcohol, Dimethicone, Acrylates/Dimethicone Copolymer, Phenoxyethanol, Glyceryl Stearate, Glycerin, Hydroxyethyl Acrylate/Sodium Acryloyldimethyl Taurate Copolymer, PEG-100 Stearate, Ceteareth-20, Ethylhexyl Salicylate, VP/Eicosene Copolymer, Xanthan Gum, Polymethyl Methacrylate, Caprylyl Glycol, Coconut (Cocos Nucifera) Oil, Ethylhexylglycerin, Vaccinium Vitis-Idaea Fruit Extract, Cork Oak (Quercus Suber) Bark Extract, Triethoxycaprylylsilane, Tea Plant (Camellia Sinensis) Leaf Extract, Disodium EDTA, Tocopheryl Acetate, Oak (Quercus) Root Extract, Gotu Kola (Centella Asiatica) Extract, Knotweed (Polygonum Aviculare) Extract, Citric Acid, Gluconolactone, Isomalt, Calcium Gluconate, Lecithin, Grape (Vitis Vinifera) Fruit Cell Extract, Sodium Benzoate, Garden Cress (Lepidium Sativum) Sprout Extract

Other Information

Protect this product from excessive heat and direct sunlight

Questions or Comments?

Questions? 1-888-256-8265 or visit www.naplessoap.com

Distributed by: Naples Soap Company • Naples, FL 33913

PRINCIPAL DISPLAY PANEL - 60 mL Bottle Label

NAPLES
SOAP COMPANY

NATURALLY BETTER
SKIN CARE

SUNSCREEN

Broad Spectrum SPF 25

25

Lightweight
Face Cream

2 fl oz (60mL)